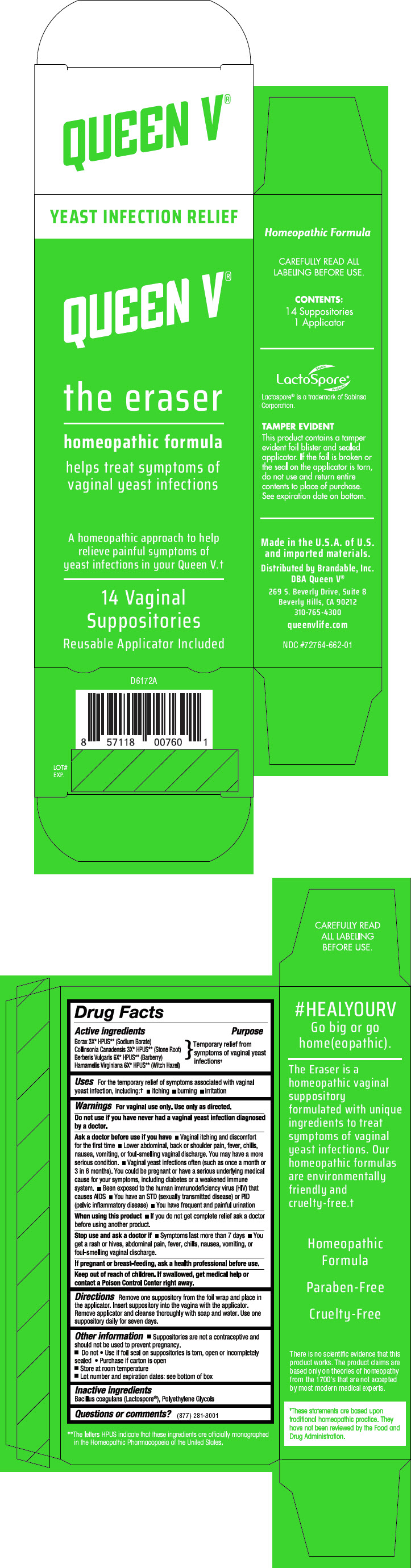 DRUG LABEL: The Eraser
NDC: 72764-003 | Form: SUPPOSITORY
Manufacturer: Brandable
Category: homeopathic | Type: HUMAN OTC DRUG LABEL
Date: 20191118

ACTIVE INGREDIENTS: Sodium Borate 3 [hp_X]/1 1; Collinsonia Canadensis Root 3 [hp_X]/1 1; Berberis Vulgaris Root Bark 6 [hp_X]/1 1; Hamamelis Virginiana Root Bark/Stem Bark 6 [hp_X]/1 1
INACTIVE INGREDIENTS: BACILLUS COAGULANS; POLYETHYLENE GLYCOL 400; POLYETHYLENE GLYCOL 1450

The Eraser

Drug Facts

Active ingredients

Borax 3X* HPUS** (Sodium Borate)
Collinsonia Canadensis 3X* HPUS** (Stone Root)
Berberis Vulgaris 6X* HPUS** (Barberry)
Hamamelis Virginiana 6X* HPUS** (Witch Hazel)

Purpose

Temporary relief from symptoms of vaginal yeast infections†

Uses

For the temporary relief of symptoms associated with vaginal yeast infection, including:†

- itching
- burning
- irritation

Warnings

For vaginal use only. Use only as directed.

Do not use if you have never had a vaginal yeast infection diagnosed by a doctor.

Ask a doctor before use if you have

- Vaginal itching and discomfort for the first time
- Lower abdominal, back or shoulder pain, fever, chills, nausea, vomiting, or foul-smelling vaginal discharge. You may have a more serious condition.
- Vaginal yeast infections often (such as once a month or 3 in 6 months). You could be pregnant or have a serious underlying medical cause for your symptoms, including diabetes or a weakened immune system.
- Been exposed to the human immunodeficiency virus (HIV) that causes AIDS
- You have an STD (sexually transmitted disease) or PID (pelvic inflammatory disease)
- You have frequent and painful urination

When using this product

- If you do not get complete relief ask a doctor before using another product.

Stop use and ask a doctor if

- Symptoms last more than 7 days
- You get a rash or hives, abdominal pain, fever, chills, nausea, vomiting, or foul-smelling vaginal discharge.

PREGNANCY OR BREAST FEEDING

If pregnant or breast-feeding, ask a health professional before use.

Keep out of reach of children. If swallowed, get medical help or contact a Poison Control Center right away.

Directions

Remove one suppository from the foil wrap and place in the applicator. Insert suppository into the vagina with the applicator. Remove applicator and cleanse thoroughly with soap and water. Use one suppository daily for seven days.

Other information

- Suppositories are not a contraceptive and should not be used to prevent pregnancy.
- Do not
  - Use if foil seal on suppositories is torn, open or incompletely sealed
  - Purchase if carton is open
- Store at room temperature
- Lot number and expiration dates: see bottom of box

Inactive ingredients

Bacillus coagulans (Lactospore®), Polyethylene Glycols

Questions or comments?

(877) 281-3001

Distributed by Brandable, Inc.
DBA Queen V®
269 S. Beverly Drive, Suite 8
Beverly Hills, CA 90212

PRINCIPAL DISPLAY PANEL - 14 Vaginal Suppositories Carton

YEAST INFECTION RELIEF

QUEEN V®

the eraser

homeopathic formula

helps treat symptoms of
vaginal yeast infections

A homeopathic approach to help
relieve painful symptoms of
yeast infections in your Queen V.†

14 Vaginal
Suppositories

Reusable Applicator Included